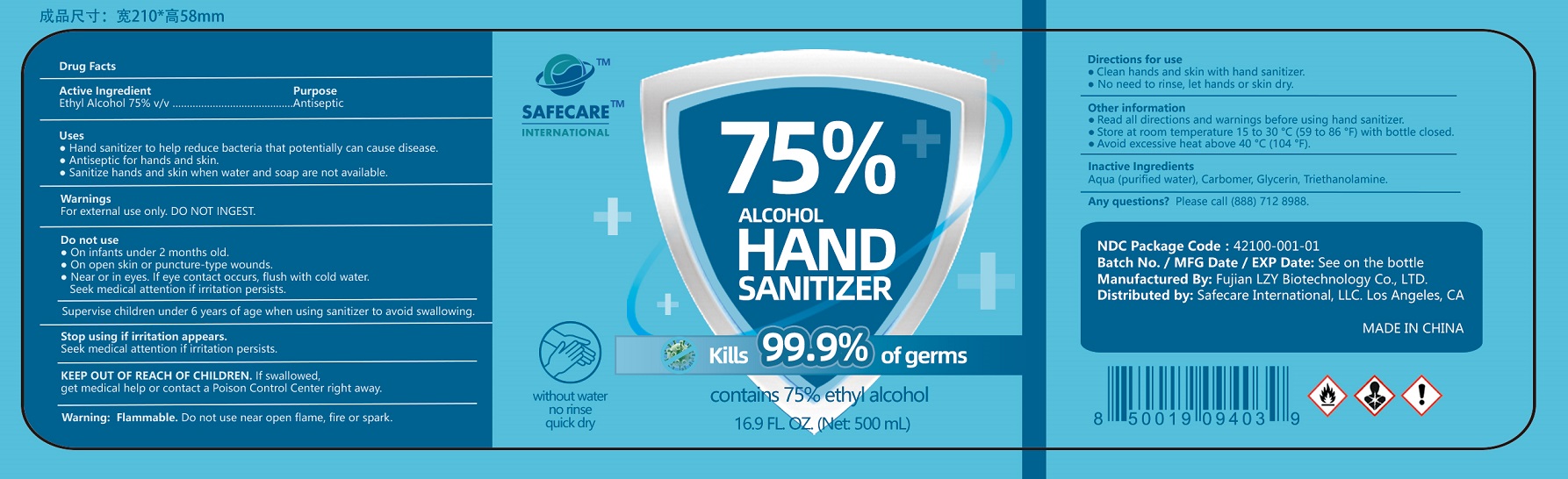 DRUG LABEL: HAND SANITIZER
NDC: 42100-001 | Form: LIQUID
Manufacturer: FUJIAN LZY BIOTECHNOLOGY CO., LTD.
Category: otc | Type: HUMAN OTC DRUG LABEL
Date: 20200917

ACTIVE INGREDIENTS: ALCOHOL 375 mL/500 mL
INACTIVE INGREDIENTS: GLYCERIN; CARBOMER HOMOPOLYMER, UNSPECIFIED TYPE; WATER; TROLAMINE

LZY, Hand Sanitizer, 75% Ethyl Alcohol, Liquid, 500mL, Bottle | Update

Active Ingredient

Ethyl Alcohol 75% v/v. Purpose: Antiseptic

Purpose

Antiseptic

Uses

● Hand sanitizer to help reduce bacteria that potentially can cause disease.
● Antiseptic for hands and skin.
● Sanitize hands and skin when water and soap are not available.

Warnings

For external use only. DO NOT INGEST.

Warning: Flammable. Do not use near open flame, fire or spark.

Do not use

● On infants under 2 months old.
● On open skin or puncture-type wounds.
● Near or in eyes. If eye contact occurs, flush with cold water.
Seek medical attention if irritation persists.

WHEN USING

Supervise children under 6 years of age when using sanitizer to avoid swallowing.

Stop using if irritation appears.
Seek medical attention if irritation persists.

KEEP OUT OF REACH OF CHILDREN

If swallowed, get medical help or contact a Poison Control Center right away.

Directions for use

● Clean hands and skin with hand sanitizer.
● No need to rinse, let hands or skin dry.

Other information

● Read all directions and warnings before using hand sanitizer.
● Store at room temperature 15 to 30 °C (59 to 86 °F) with bottle closed.
● Avoid excessive heat above 40 °C (104 °F).

Inactive ingredients

Aqua (purified water), Carbomer, Glycerin, Triethanolamine.

Any questions?

Please call (888) 712 8988.